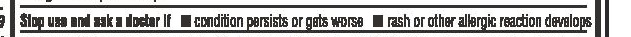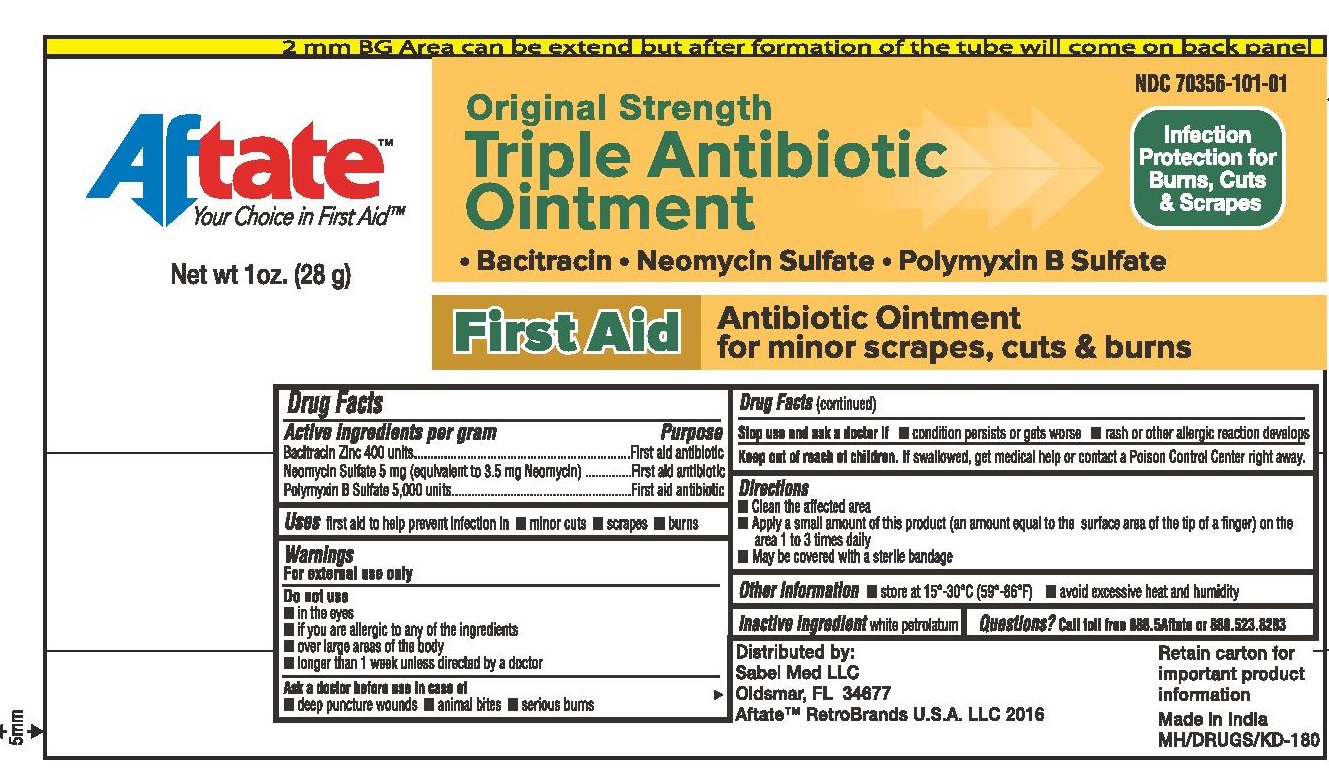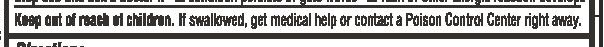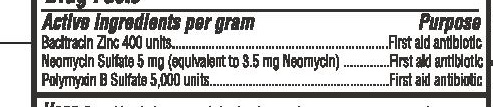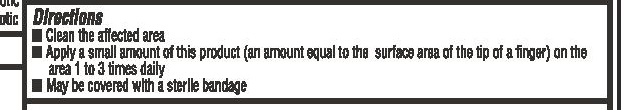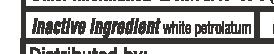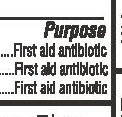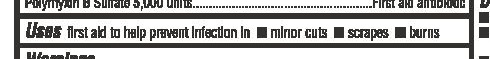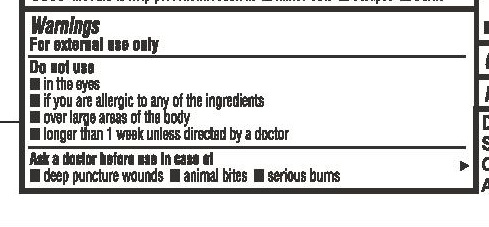 DRUG LABEL: Aftate Triple Antibiotic
NDC: 70356-101 | Form: OINTMENT
Manufacturer: Sabel Med LLC
Category: otc | Type: HUMAN OTC DRUG LABEL
Date: 20160401

ACTIVE INGREDIENTS: POLYMYXIN B SULFATE 5000 [iU]/1 g; NEOMYCIN SULFATE 3.5 mg/1 g; BACITRACIN ZINC 400 [iU]/1 g
INACTIVE INGREDIENTS: PETROLATUM

Triple Antibiotic Ointment